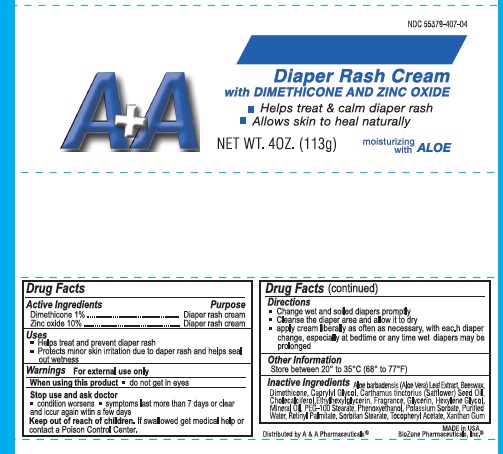 DRUG LABEL: A AND A Diaper Rash cream 
NDC: 55379-407 | Form: CREAM
Manufacturer: BioZone Laboratories, Inc.
Category: otc | Type: HUMAN OTC DRUG LABEL
Date: 20130714

ACTIVE INGREDIENTS: DIMETHICONE 10 mg/1 g; ZINC OXIDE 100 mg/1 g
INACTIVE INGREDIENTS: ALOE VERA LEAF; YELLOW WAX; CAPRYLYL GLYCOL; SAFFLOWER OIL; CHOLECALCIFEROL; ETHYLHEXYLGLYCERIN; GLYCERIN; HEXYLENE GLYCOL; MINERAL OIL; PEG-100 STEARATE; PHENOXYETHANOL; POTASSIUM SORBATE; WATER; VITAMIN A PALMITATE; SORBITAN MONOSTEARATE; .ALPHA.-TOCOPHEROL ACETATE; XANTHAN GUM

ACTIVE INGREDIENT

Active ingredients | Purpose
Dimethicone 1% | Diaper rash Cream
Zinc Oxide 10% | Diaper rash Cream

Uses

- helps treat and prevent diaper rash
- protects minor skin irritation due to diaper rash and helps seal out wetness

Warnings

For external use only

When using this product

- do not get into eyes

Stop use and ask a doctor if

- condition worsens
- symptoms last more than 7 days or clear up and occur again within a few days

Keep out of reach of children. If swallowed, get medical help or contact a Poison Control Center right away.

Directions

- change wet and soiled diapers promptly
- cleanse the diaper area, and allow to dry
- apply cream liberally as often as necessary, with each diaper change, especially at bedtime or anytime when exposure to wet diapers may be prolonged

Other information

store between 20°C to 25 °C (68° to 77°F)

Inactive Ingredients

Aloe barbadensis extract, benzyl alcohol, coconut oil, cod liver oil (contains vitamin A & Vitamin D), fragrance, glyceryl oleate, light mineral oil, ozokerite, paraffin, propylene glycol, sorbitol, synthetic beeswax, water

Principal Display Panel

A+A Diaper Rash Cream

with DIMETHICONE AND ZINC OXIDE

Helps treat and calm diaper rash

Allows Skin to heal naturally

A+A Diaper Rash Cream